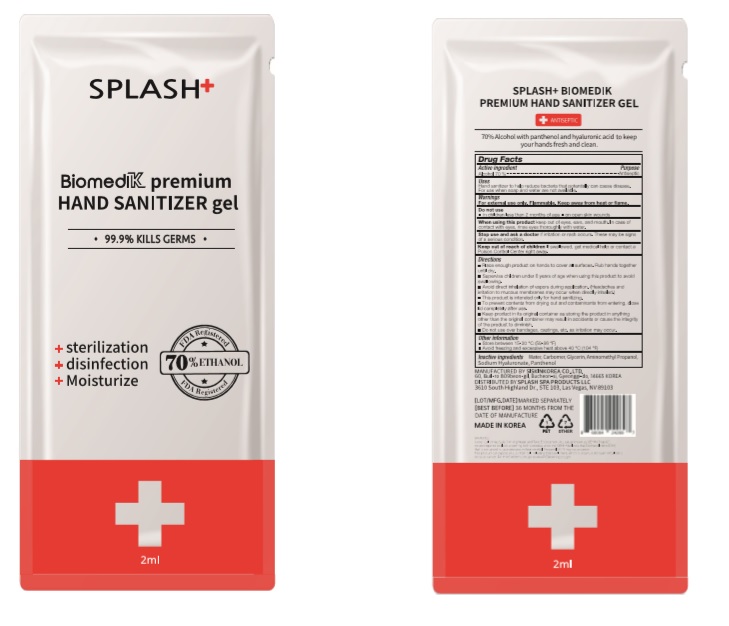 DRUG LABEL: BiomediK Premium Hand Sanitizer gel
NDC: 74514-0002 | Form: GEL
Manufacturer: SISKINKOREA CO.,LTD.
Category: otc | Type: HUMAN OTC DRUG LABEL
Date: 20200708

ACTIVE INGREDIENTS: ALCOHOL 1.4 mL/2 mL
INACTIVE INGREDIENTS: CARBOMER HOMOPOLYMER, UNSPECIFIED TYPE; AMINOMETHYLPROPANOL; GLYCERIN; PANTHENOL; WATER; HYALURONATE SODIUM

BiomediK Premium Hand Sanitizer gel | POUCH | 74514-0002-1